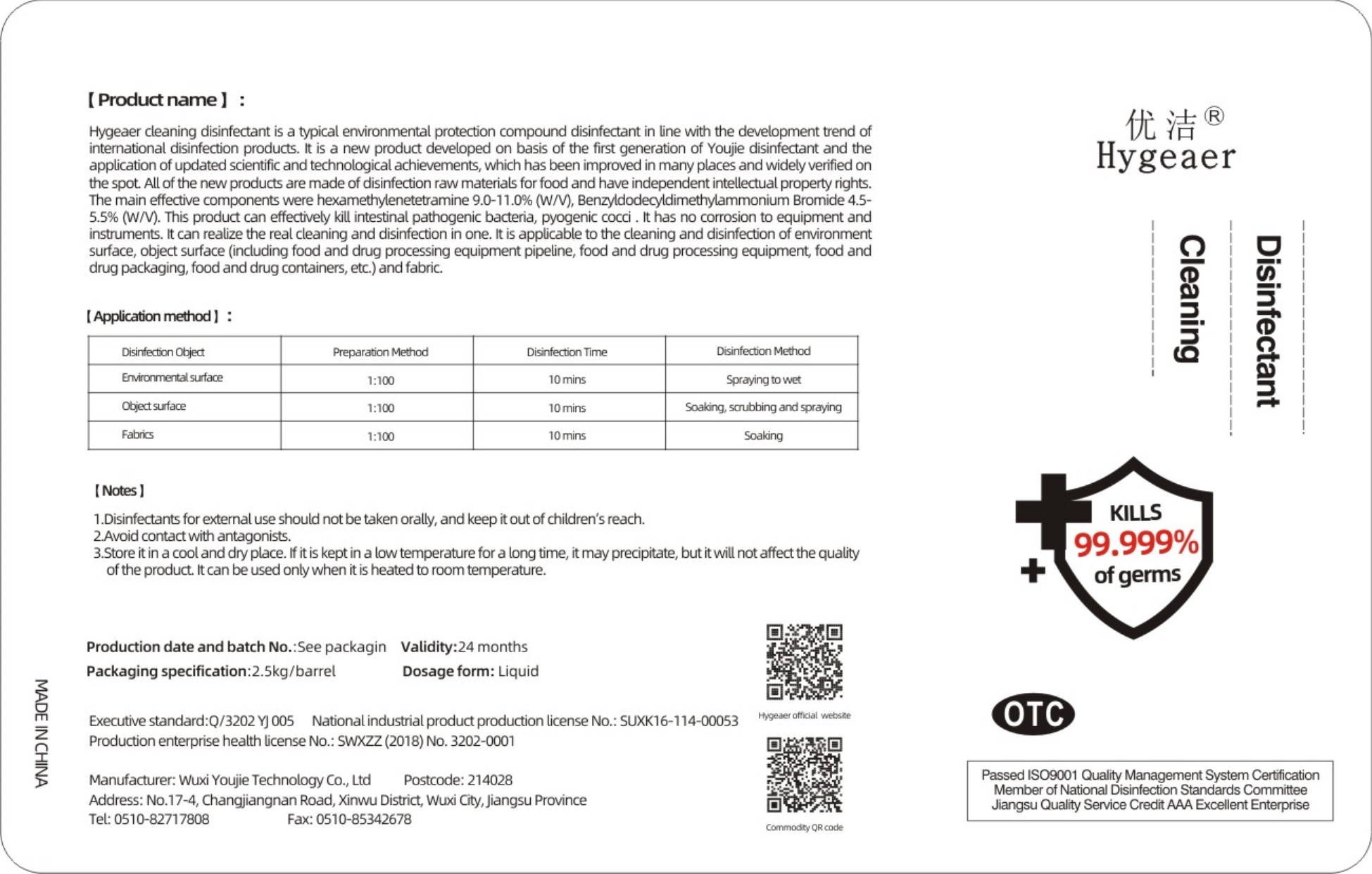 DRUG LABEL: Cleaning Disinfectant
NDC: 54796-003 | Form: LIQUID
Manufacturer: Wuxi Youjie Technology Co. LTD
Category: otc | Type: HUMAN OTC DRUG LABEL
Date: 20200428

ACTIVE INGREDIENTS: METHENAMINE 250 g/2500 g; BENZALKONIUM BROMIDE 125 g/2500 g
INACTIVE INGREDIENTS: WATER

DOSAGE AND ADMINISTRATION

Store itin a cool and dry place.

INACTIVE INGREDIENT

water

INDICATIONS AND USAGE

Enviironmental suface:10 mins Spraying to wet.

Object surface: 10 mins Soaking soubbing and spraying.

Fabrics:10 mins Soaking

ACTIVE INGREDIENT

BENZALKONIUM BROMIDE

HEXAMETHYLENETETRAMINE

keep out of reach of children

PURPOSE

Disinfection
Sterilization

WARNINGS

1.Disinfectants for extermal use should not be taken orally, and keepit out of children's reach.
2 Avoid contact with antagonists.
3.Store itin a cool and dry place. If itis keptin a low temperature for a long time, itmay precipitate, but itwill not affect the quality of the product. Itcan be used onlywhen it is heated to room temperature.